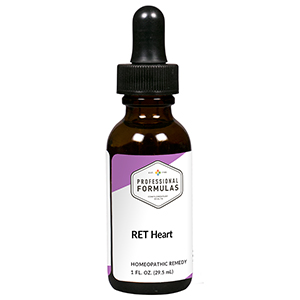 DRUG LABEL: RET Heart
NDC: 63083-7009 | Form: LIQUID
Manufacturer: Professional Complementary Health Formulas
Category: homeopathic | Type: HUMAN OTC DRUG LABEL
Date: 20190815

ACTIVE INGREDIENTS: FAGUS SYLVATICA FLOWERING TOP 3 [hp_X]/29.5 mL; IMPATIENS GLANDULIFERA FLOWER 3 [hp_X]/29.5 mL; VERBENA OFFICINALIS FLOWERING TOP 3 [hp_X]/29.5 mL; POTASSIUM PHOSPHATE, UNSPECIFIED FORM 3 [hp_X]/29.5 mL; MAGNESIUM PHOSPHATE, DIBASIC TRIHYDRATE 3 [hp_X]/29.5 mL; SILICON DIOXIDE 3 [hp_X]/29.5 mL; ACONITUM NAPELLUS WHOLE 30 [hp_X]/29.5 mL; GOLD 30 [hp_X]/29.5 mL; CAUSTICUM 30 [hp_X]/29.5 mL; COFFEA ARABICA SEED, ROASTED 30 [hp_X]/29.5 mL; SAFFRON 30 [hp_X]/29.5 mL; PULSATILLA MONTANA WHOLE 30 [hp_X]/29.5 mL
INACTIVE INGREDIENTS: ALCOHOL; WATER

RET9

ACTIVE INGREDIENTS

Beech flower essence 3X
Impatiens flower essence 3X
Vervain flower essence 3X
Kali phosphoricum 3X, 6X, 30X
Magnesia phosphorica 3X, 6X, 30X
Silicea 3X, 6X, 30X
and all the following at 30X, 100X, 200X:
Aconitum napellus
Aurum metallicum
Causticum
Coffea tosta
Crocus sativus
Pulsatilla

QUESTIONS

Professional Formulas

PO Box 2034 Lake Oswego, OR 97035

INDICATIONS

Temporarily relieves indifference, intolerance, impatience, irritation, overenthusiasm, hyperactivity, dread, sadness, or anxiousness.*

PURPOSE

*Claims based on traditional homeopathic practice, not accepted medical evidence. Not FDA evaluated.

WARNINGS

In case of overdose, get medical help or contact a poison control center right away.

Keep out of the reach of children.

PREGNANCY OR BREAST FEEDING

If pregnant or breastfeeding, ask a healthcare professional before use.

DIRECTIONS

Place drops under tongue 30 minutes before/after meals. Adults and children 12 years and over: Take 5 drops up to 4 times per day for up to one month. Consult a physician for use in children under 12 years of age.

OTHER INFORMATION

Tamper resistant. If seal is broken, do not use. After opening, close container tightly and store at room temperature away from heat.

INACTIVE INGREDIENTS

20% ethanol, purified water.

LABEL

Est 1985

Professional Formulas

Complementary Health

RET Heart

Homeopathic Remedy

1 FL. OZ. (29.5 mL)